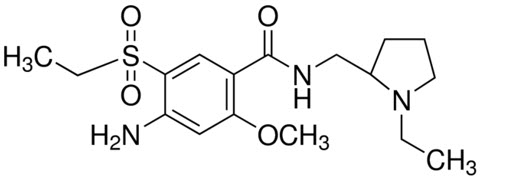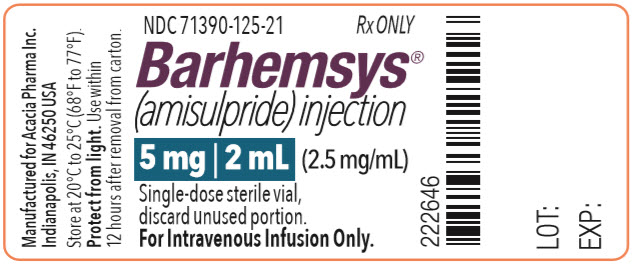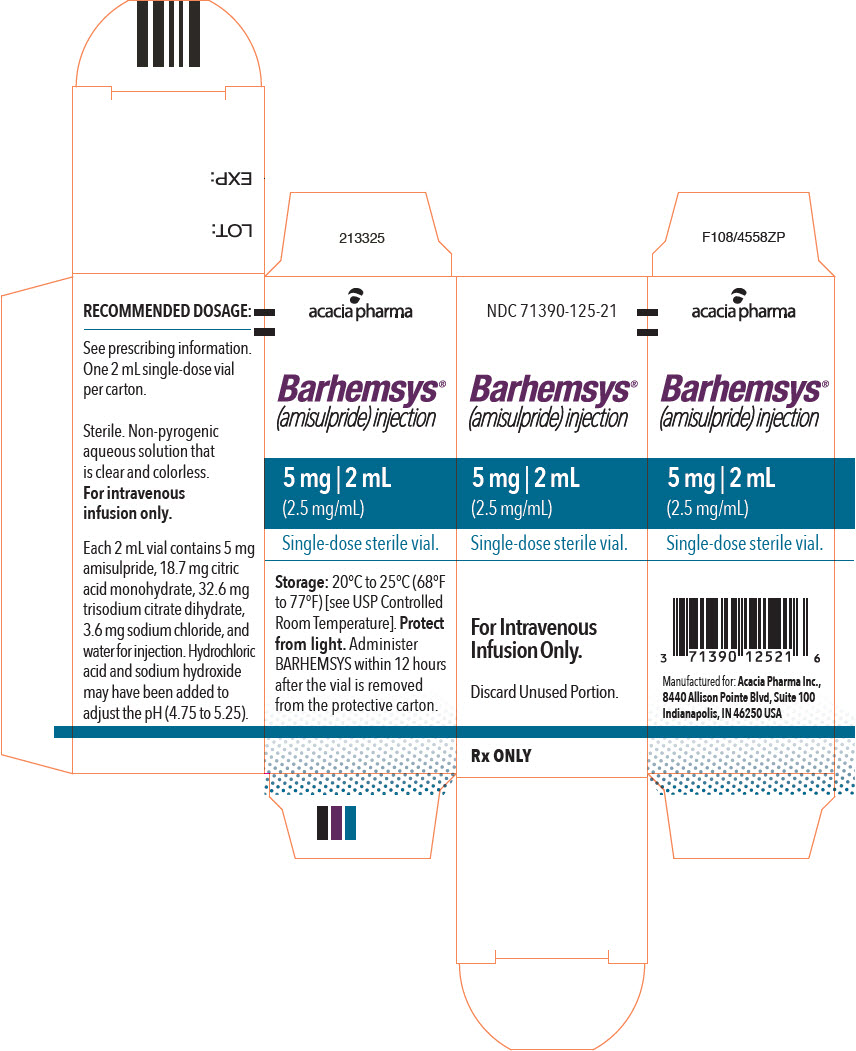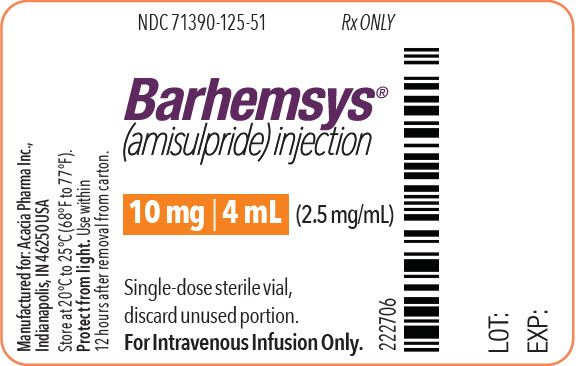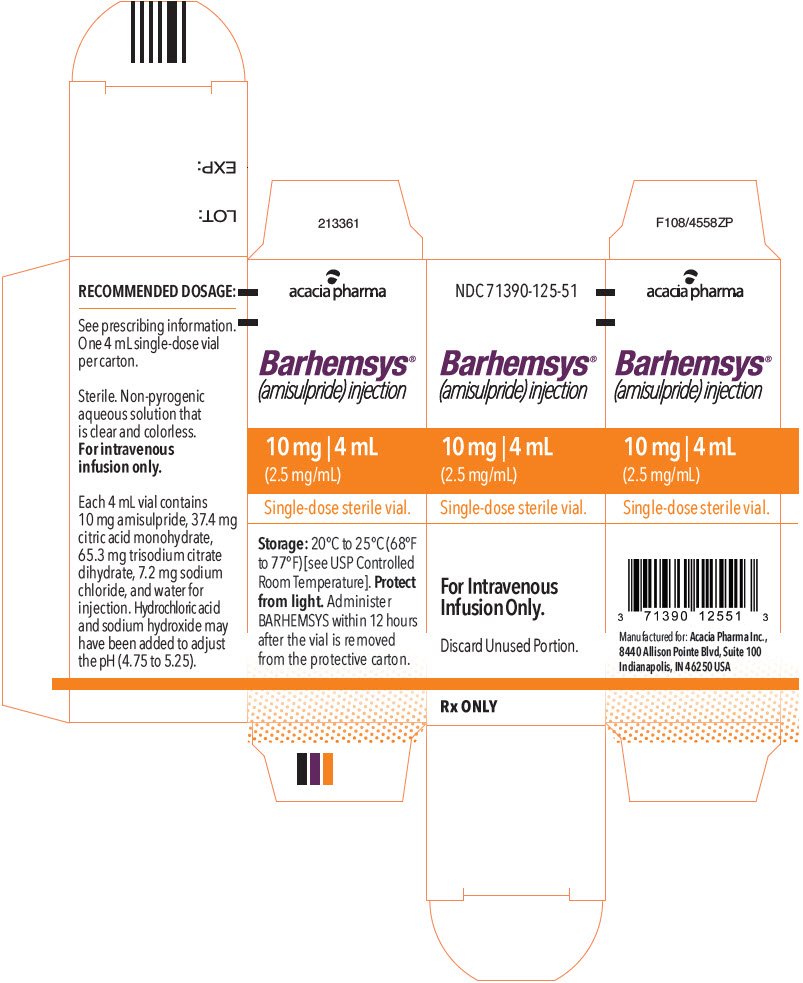 DRUG LABEL: Barhemsys
NDC: 71390-125 | Form: INJECTION, SOLUTION
Manufacturer: Acacia Pharma Ltd
Category: prescription | Type: HUMAN PRESCRIPTION DRUG LABEL
Date: 20250609

ACTIVE INGREDIENTS: Amisulpride 2.5 mg/1 mL
INACTIVE INGREDIENTS: Citric Acid Monohydrate; Sodium Chloride; Trisodium Citrate Dihydrate; Hydrochloric Acid; Sodium Hydroxide

HIGHLIGHTS OF PRESCRIBING INFORMATION

These highlights do not include all the information needed to use BARHEMSYS safely and effectively. See full prescribing information for BARHEMSYS.
BARHEMSYS® (amisulpride) injection, for intravenous use
Initial U.S. Approval: 2020

1 INDICATIONS AND USAGE

BARHEMSYS is a dopamine-2 (D2) antagonist indicated in adults for:

- Prevention of postoperative nausea and vomiting (PONV), either alone or in combination with an antiemetic of a different class. (1)
- Treatment of PONV in patients who have received antiemetic prophylaxis with an agent of a different class or have not received prophylaxis. (1)

2 DOSAGE AND ADMINISTRATION

The recommended dosage of BARHEMSYS:

- Prevention of PONV, either alone or in combination with another antiemetic: 5 mg as a single intravenous dose infused over 1 to 2 minutes at the time of induction of anesthesia. (2.1)
- Treatment of PONV: 10 mg as a single intravenous dose infused over 1 to 2 minutes in the event of nausea and/or vomiting after a surgical procedure. (2.1)
- See full prescribing information for preparation and administration instructions. (2.2)

3 DOSAGE FORMS AND STRENGTHS

Injection: 5 mg/2 mL (2.5 mg/mL) or 10 mg/4 mL (2.5 mg/mL) in a single-dose vial. (3)

4 CONTRAINDICATIONS

Known hypersensitivity to amisulpride. (4)

5 WARNINGS AND PRECAUTIONS

QT Prolongation: Occurs in a dose- and concentration-dependent manner. Avoid use in patients with congenital long QT syndrome and in patients taking droperidol. ECG monitoring is recommended in patients with pre-existing arrhythmias/cardiac conduction disorders; electrolyte abnormalities (e.g., hypokalemia or hypomagnesemia); congestive heart failure; and in patients taking other medicinal products (e.g., ondansetron) or with other medical conditions known to prolong the QT interval. (5.1, 7.2)

6 ADVERSE REACTIONS

Most common adverse reactions (≥ 2%) are:

- Prevention of PONV: increased blood prolactin concentrations, chills, hypokalemia, procedural hypotension, and abdominal distension. (6.1)
- Treatment of PONV: infusion site pain. (6.1)

To report SUSPECTED ADVERSE REACTIONS, contact Acacia Pharma at 1-877-357-9237 or FDA at 1-800-FDA-1088 or www.fda.gov/medwatch.

8 USE IN SPECIFIC POPULATIONS

Lactation: A lactating woman may pump and discard breast milk for 48 hours after BARHEMSYS administration. (8.2)

FULL PRESCRIBING INFORMATION

1 INDICATIONS AND USAGE

BARHEMSYS® is indicated in adults for:

- prevention of postoperative nausea and vomiting (PONV), either alone or in combination with an antiemetic of a different class.
- treatment of PONV in patients who have received antiemetic prophylaxis with an agent of a different class or have not received prophylaxis.

2 DOSAGE AND ADMINISTRATION

2.1 Recommended Dosage

The recommended adult dosage of BARHEMSYS and infusion rate by indication is shown in the table below:

Indication | Adult Dosage Regimen
Prevention of PONV | 5 mg as a single intravenous injection infused over 1 to 2 minutes at the time of induction of anesthesia [see Dosage and Administration (2.2)].
Treatment of PONV | 10 mg as a single intravenous injection infused over 1 to 2 minutes in the event of nausea and/or vomiting after a surgical procedure [see Dosage and Administration (2.2)].

2.2 Preparation and Administration

- Dilution of BARHEMSYS is not required before administration. BARHEMSYS is chemically and physically compatible with Water for Injection, 5% Dextrose Injection, 0.9% Sodium Chloride Injection, and Lactated Ringer's Solution (also known as Ringer's Lactate Solution, Compound Sodium Lactate Solution, and Hartmann's Solution), any of which may be used to flush an intravenous line before or after administration of BARHEMSYS.
- Protect from light. BARHEMSYS is subject to photodegradation. Administer BARHEMSYS within 12 hours of removal of the vial from the protective carton.
- Prior to administration, inspect the BARHEMSYS solution visually for particulate matter and discoloration. Discard if particulate matter or discoloration is observed.

3 DOSAGE FORMS AND STRENGTHS

Injection: 5 mg/2 mL (2.5 mg/mL) or 10 mg/4 mL (2.5 mg/mL) as a clear, colorless sterile solution in a single-dose vial.

4 CONTRAINDICATIONS

BARHEMSYS is contraindicated in patients with known hypersensitivity to amisulpride [see Adverse Reactions (6.2)].

5 WARNINGS AND PRECAUTIONS

5.1 QT Prolongation

BARHEMSYS causes dose- and concentration-dependent prolongation of the QT interval [see Clinical Pharmacology (12.2)]. The recommended dosage is 5 or 10 mg as a single intravenous dose infused over 1 to 2 minutes [see Dosage and Administration (2.1)].

Avoid use in patients with congenital long QT syndrome and in patients taking droperidol.

Electrocardiogram (ECG) monitoring is recommended in patients with pre-existing arrhythmias/cardiac conduction disorders; electrolyte abnormalities (e.g., hypokalemia or hypomagnesemia); congestive heart failure; and in patients taking other medicinal products (e.g., ondansetron) or with other medical conditions known to prolong the QT interval [see Drug Interactions (7.2)].

6 ADVERSE REACTIONS

6.1 Clinical Trials Experience

Because clinical trials are conducted under widely varying conditions, adverse reaction rates observed in the clinical trials of a drug cannot be directly compared to rates in the clinical trials of another drug and may not reflect the rates observed in practice.

The data described below reflect exposure to BARHEMSYS in 1,166 patients treated in placebo-controlled trials. 748 of these patients received a dose of 5 mg for prevention of PONV (of whom 572 received another antiemetic concomitantly) and 418 patients received 10 mg for treatment of PONV [see Clinical Studies (14.1, 14.2)]. The mean age of the population was 49 years (range 18 to 91 years), 87% female, 80% White/Caucasian, 9% Black, and 1% Asian.

Prevention of PONV

Common adverse reactions reported in at least 2% of adult patients who received BARHEMSYS 5 mg and at a higher rate than placebo in Studies 1 and 2 for the prevention of PONV are shown in Table 1.

Table 1. Common Adverse Reactions [Reported in at least 2% of patients treated with BARHEMSYS and at a higher rate than placebo] in Adult Patients in Studies 1 and 2 of BARHEMSYS for Prevention of PONV
 | BARHEMSYS 5 mg | Placebo
 | N=748 | N=741
Chills | 4% | 3%
Hypokalemia | 4% | 2%
Procedural hypotension | 3% | 2%
Abdominal distension | 2% | 1%

Serum prolactin concentrations were measured in Study 1 where 5% (9/176) of BARHEMSYS-treated patients vs 1% (1/166) of placebo-treated patients had increased blood prolactin reported as an adverse reaction. Serum prolactin concentrations increased from a mean of 10 ng/mL at baseline to 32 ng/mL after BARHEMSYS treatment in 112 females (upper limit of normal 29 ng/mL) and from 10 ng/mL to 19 ng/mL in 61 males (upper limit of normal 18 ng/mL). No clinical consequences due to elevated prolactin levels were reported.

Treatment of PONV

The most common adverse reaction, reported in at least 2% of adult patients who received BARHEMSYS 10 mg (N=418) and at a higher rate than placebo (N=416), in clinical trials for the treatment of PONV (Studies 3 and 4) was infusion site pain (BARHEMSYS 6%; placebo 4%).

6.2 Postmarketing Experience

The following adverse reactions have been identified during post-approval chronic oral use of amisulpride outside of the United States (BARHEMSYS is not approved for oral dosing or chronic use). Because these reactions are reported voluntarily from a population of uncertain size, it is not always possible to reliably estimate their frequency or establish a causal relationship to drug exposure.

- Blood and lymphatic system disorders: agranulocytosis
- Cardiac disorders: bradycardia, torsades de pointes, ventricular tachycardia, prolonged QT by electrocardiogram
- General disorders: neuroleptic malignant syndrome
- Immune system disorders: angioedema, hypersensitivity, urticaria
- Hepatic disorders: increased hepatic enzymes
- Nervous system disorders: agitation, anxiety, dystonia, extrapyramidal disorder, seizure
- Psychiatric disorders: confusional state, insomnia, somnolence
- Vascular disorders: hypotension

7 DRUG INTERACTIONS

7.1 Dopamine Agonists

Reciprocal antagonism of effects occurs between dopamine agonists (e.g., levodopa) and BARHEMSYS. Avoid using levodopa with BARHEMSYS.

7.2 Drugs Prolonging the QT Interval

BARHEMSYS causes dose- and concentration-dependent QT prolongation [see Clinical Pharmacology (12.2)]. To avoid potential additive effects, avoid use of BARHEMSYS in patients taking droperidol. ECG monitoring is recommended in patients taking other drugs known to prolong the QT interval (e.g., ondansetron) [see Warnings and Precautions (5.1)].

8 USE IN SPECIFIC POPULATIONS

8.1 Pregnancy

Risk Summary

Available data with amisulpride use in pregnant women are insufficient to establish a drug associated risk of major birth defects, miscarriage or adverse maternal or fetal outcomes. In animal reproduction studies, there were no adverse developmental effects observed with oral administration of amisulpride in rats and rabbits during the period of organogenesis at exposures about 43 and 645 times, respectively, the exposure delivered by the highest recommended human dose (see Data).

The estimated background risk of major birth defects and miscarriage for the indicated population is unknown. All pregnancies have a background risk of birth defect, loss, or other adverse outcomes. In the U.S. general population, the estimated background risk of major birth defects and miscarriage in clinically recognized pregnancies is 2% to 4% and 15% to 20%, respectively.

Data

Animal Data

Reproduction studies of amisulpride were conducted in pregnant rats administered oral doses up to 160 mg/kg/day (43 times the exposure based on area under the curve (AUC) at the highest recommended dose of 10 mg) throughout the period of organogenesis. No adverse embryo-fetal developmental effects were observed at any dose level. Maternal animals exhibited a dose-related decrease in overall mean body weight gain. In rabbits administered amisulpride throughout the period of organogenesis, oral doses up to 210 mg/kg/day (645 times the exposure based on AUC at the highest recommended dose of 10 mg) had no adverse developmental effects on the fetus. Maternal animals exhibited reduced mean body weight gain at doses of 100 and 210 mg/kg/day and reduced food intake was observed at 210 mg/kg/day.

The pre- and post-natal developmental effects of amisulpride were assessed in rats administered oral doses of 60, 100 or 160 mg/kg/day during the periods of organogenesis and lactation. At 160 mg/kg/day (43 times the exposure based on AUC at the highest recommended dose of 10 mg), maternal animals exhibited a reduction in mean body weight gain and decrease in food intake during lactation. Amisulpride had no effect on maternal pregnancy parameters, litter survival or pup growth, development or maturation at any dose tested.

8.2 Lactation

Risk Summary

Based on case reports in published literature, amisulpride is present in human milk at concentrations that are 11- to 20-fold higher than human plasma in patients taking multiple oral doses of amisulpride (200 to 400 mg/day). The estimated infant daily dose ranged from 5% to 11% of the maternal dose. There are ways to minimize drug exposure to a breastfed infant (see Clinical Considerations). There are no reports of adverse effects on the breastfed child and no information on the effects of amisulpride on milk production. The pharmacological action of amisulpride, a dopamine-2 (D2) receptor antagonist, may result in an increase in serum prolactin levels, which may lead to a reversible increase in maternal milk production [see Adverse Reactions (6.1)]. The developmental and health benefits of breastfeeding should be considered along with the mother's clinical need for BARHEMSYS and any potential adverse effects on the breastfed child from BARHEMSYS or from the underlying maternal condition.

Clinical Considerations

A lactating woman may consider interrupting breastfeeding and pumping and discarding breast milk for 48 hours after BARHEMSYS administration to minimize drug exposure to a breastfed infant.

8.3 Females and Males of Reproductive Potential

Infertility

In animal fertility studies, administration of repeated doses of amisulpride over a 10-day period to female rats resulted in infertility that was reversible [see Nonclinical Toxicology (13.1)].

8.4 Pediatric Use

Safety and effectiveness in pediatric patients have not been established.

8.5 Geriatric Use

Of the total number of patients enrolled in controlled clinical trials who received BARHEMSYS 5 mg for prevention of PONV or 10 mg for treatment of PONV, 235 (17%) were 65 years of age and older, while 59 (4%) were 75 years of age and older. No overall differences in safety or effectiveness were observed between these patients and younger patients, and other reported clinical experience has not identified differences in responses between the elderly and younger patients, but greater sensitivity of some older individuals cannot be ruled out.

10 OVERDOSAGE

Doses of oral amisulpride (BARHEMSYS is not approved for oral dosing) above 1200 mg/day have been associated with adverse reactions related to dopamine-2 (D2) antagonism, in particular:

- cardiovascular adverse reactions (e.g., prolongation of the QT interval, torsades de pointes, bradycardia and hypotension) [see Warnings and Precautions (5.1)].
- neuropsychiatric adverse reactions (e.g., sedation, coma, seizures, and dystonic and extrapyramidal reactions).

There is no specific antidote for amisulpride overdose. Management includes cardiac monitoring and treatment of severe extrapyramidal symptoms.

Since amisulpride is weakly dialyzed, hemodialysis should not be used to eliminate the drug.

11 DESCRIPTION

The active ingredient of BARHEMSYS is amisulpride, a dopamine-2 (D2) receptor antagonist. Its chemical name is 4-Amino-N-[(1-ethyl-2-pyrrolidinyl)methyl]-5-(ethylsulfonyl)-o-anisamide. It has the following chemical structure:

(racemic)

The empirical formula is C17H27N3O4S representing a molecular weight of 369.48.

Amisulpride is a white or almost white crystalline powder. It is practically insoluble in water, sparingly soluble in ethanol and freely soluble in methylene chloride, and has a melting point of around 126°C. The compound is racemic and shows no optical rotation and is not hygroscopic. No other polymorphs of amisulpride have been reported.

BARHEMSYS (amisulpride) injection is a clear, colorless, nonpyrogenic, sterile solution formulation of amisulpride 5 mg/2 mL (2.5 mg/mL) or 10 mg/4 mL (2.5 mg/mL) for intravenous infusion presented in a single-dose vial. It has a pH of approximately 5.0 and the osmolality of the product is between 250 and 330 mOsmol/kg.

Each 2 mL vial of BARHEMSYS contains 5 mg of amisulpride; 18.7 mg of citric acid monohydrate USP; 3.6 mg of sodium chloride USP; 32.64 mg of trisodium citrate dihydrate; hydrochloric acid NF and sodium hydroxide NF as needed to adjust the pH (4.75 to 5.25); and Water for Injection USP to make up to volume.

Each 4 mL vial of BARHEMSYS contains 10 mg of amisulpride; 37.4 mg of citric acid monohydrate USP; 7.2 mg of sodium chloride USP; 65.3 mg of trisodium citrate dihydrate; hydrochloric acid NF and sodium hydroxide NF as needed to adjust the pH (4.75 to 5.25); and Water for Injection USP to make up to volume.

12 CLINICAL PHARMACOLOGY

12.1 Mechanism of Action

Amisulpride is a selective dopamine-2 (D2) and dopamine-3 (D3) receptor antagonist. D2 receptors are located in the chemoreceptor trigger zone (CTZ) and respond to the dopamine released from the nerve endings. Activation of CTZ relays stimuli to the vomiting center which is involved in emesis. Studies in multiple species indicate that D3 receptors in the area postrema also play a role in emesis. Studies conducted in ferrets have shown that amisulpride inhibits emesis caused by apomorphine, with an estimated ED50 of less than 1 mcg/kg, subcutaneously; and inhibits cisplatin-induced emesis at 2 mg/kg and morphine-induced emesis at 3 to 6 mg/kg, when given intravenously.

Amisulpride has no appreciable affinity for any other receptor types apart from low affinities for 5-HT2B and 5-HT7 receptors.

12.2 Pharmacodynamics

Cardiac Electrophysiology

A significant exposure-response relationship was identified between amisulpride concentration and ΔΔQTcF. In 40 healthy Caucasian and Japanese subjects, the maximum mean difference (95% upper confidence bound) in QTcF from placebo after baseline-correction (ΔΔQTcF) was 5.0 (7.1) milliseconds after a 2-minute intravenous infusion of 5 mg BARHEMSYS and 23.4 (25.5) milliseconds after an 8-minute intravenous infusion of 40 mg BARHEMSYS [see Warnings and Precautions (5.1)].

The recommended infusion rate is 1 to 2 minutes for 5 mg or 10 mg of BARHEMSYS [see Dosage and Administration (2.1)].

12.3 Pharmacokinetics

After an intravenous infusion, the peak plasma concentration of amisulpride is achieved at the end of the infusion period and the plasma concentration decreases to about 50% of the peak value within approximately 15 minutes. The AUC(0-∞) increases dose-proportionally in the dose range from 5 mg to 40 mg (4-times the maximum recommended dose).

The following mean pharmacokinetic parameters of amisulpride were observed following a single 5 or 10 mg intravenous dose in adult healthy subjects and surgical patients.

Table 2. Summary of Key Pharmacokinetic Parameters of Amisulpride from Clinical Studies
 | Single Dose | Infusion Duration (minutes) | Number of Subjects | Mean (SD)
 | Single Dose | Infusion Duration (minutes) | Number of Subjects | Peak Plasma Concentration (ng/mL) | AUC(0-∞) (ng∙h/mL)
Healthy Subjects | 5 mg | 2 | 39 | 200 (139) | 154 (30)
Healthy Subjects | 10 mg | 1 | 29 | 451 (230) | 136 (28) [AUC(0-2 hr)]
Patients | 5 mg | 1 to 2 | 26 [Patients in a clinical trial for prophylaxis of PONV] | 161 (58) | 260 (65)
Patients | 5 mg | 1 to 2 | 27 [Patients in clinical trials for treatment of PONV] | 127 (64) | 204 (94)
Patients | 10 mg | 1 to 2 | 31 | 285 (446) | 401 (149)

Distribution

Following intravenous infusion, the mean volume of distribution of amisulpride is estimated to be 127 to 144 L in surgical patients and 171 L in healthy subjects.

Amisulpride distributes into erythrocytes. Plasma protein binding is 25% to 30% in the concentration range from 37 to 1850 ng/mL.

Elimination

The mean elimination half-life is approximately 4 to 5 hours and similar between healthy subjects and surgical patients. Population pharmacokinetic analysis estimated that the plasma clearance of amisulpride is 20.6 L/h in surgical patients and 24.1 L/h in healthy subjects.

Metabolism

In a mass balance study, no metabolites were detectable in plasma while four metabolites were identified in urine and feces. Each metabolite accounts for less than 7% of the dose. In vitro amisulpride is not metabolized by major cytochrome P450 enzymes.

Excretion

After intravenous administration of amisulpride, 74% and 23% of the administered dose was recovered in urine and feces, respectively. 58% and 20% of the dose was excreted as unchanged amisulpride in urine and feces, respectively.

Renal clearance was estimated to be 20.5 L/hr (342 mL/min) in healthy subjects suggesting that amisulpride undergoes active renal secretion.

Specific Populations

Age, Sex, and Racial Groups

No clinically significant effect on the pharmacokinetics of amisulpride was observed based on age (18 to 90 years), sex, or race.

Patients with Renal Impairment

In subjects with severe renal impairment (eGFR < 30 mL/min/1.73 m^2) and no requirement for dialysis, the Cmax of amisulpride after a single 10 mg intravenous dose was not greater than that in healthy subjects with normal renal function, and the AUC(0-∞) was approximately twice as high.

In surgical patients with mild or moderate renal impairment (eGFR 30 to 89 mL/min/1.73 m^2), the Cmax of amisulpride following a single 5 mg or 10 mg intravenous dose was not significantly different and the AUC(0-∞) of amisulpride increased about 1.3-fold compared to patients with normal renal function.

The changes in the pharmacokinetics of amisulpride following a single 5 mg or 10 mg intravenous dose in subjects or patients with mild, moderate, or severe renal impairment compared to subjects or patients with normal renal function are not considered to be clinically meaningful.

Drug Interaction Studies

No clinical drug interaction trials have been conducted with BARHEMSYS.

In Vitro Studies

Cytochrome P450-Related Metabolism

In vitro, amisulpride did not inhibit CYP1A2, CYP2A6, CYP2B6, CYP2C9, CYP2C19, CYP2D6, or CYP3A4, or induce CYP1A2, CYP2C9, CYP2C19, or CYP3A4.

In vitro, amisulpride was not a substrate of CYP1A2, CYP2A6, CYP2B6, CYP2C8, CYP2C9, CYP2C19, CYP2D6, CYP2E1 and CYP3A4.

Transporters

Amisulpride inhibits MATE1 and MATE2-K transporters.

Amisulpride does not inhibit P-gp, BCRP, OCT1, OCT2, OAT1, OAT3, OATP1B1, OATP1B3 at therapeutic concentrations.

Amisulpride is a substrate for P-gp, BCRP, OCT1, MATE1 and MATE2-K, but not a substrate for OATP1B1, OATP1B3, OAT1, OAT3 and OCT2.

13 NONCLINICAL TOXICOLOGY

13.1 Carcinogenesis, Mutagenesis, Impairment of Fertility

Long-term studies to assess the carcinogenic potential of amisulpride have not been conducted. Amisulpride was not genotoxic in the bacterial reverse mutation assay, the in vitro human peripheral blood lymphocytes assay, and the in vivo rat bone marrow micronucleus assay.

The effect of amisulpride on fertility was studied in rats at oral doses up to 160 mg/kg/day (43 times the exposure based on AUC at the highest recommended dose of 10 mg). Most female animals (90% to 95%) at each dose level remained in diestrus and failed to mate. However, this effect on mating reversed following cessation of treatment. No treatment-related effects were observed on uterine/implantation parameters or sperm counts, sperm motility or sperm morphology.

14 CLINICAL STUDIES

14.1 Prevention of Postoperative Nausea and Vomiting

The efficacy of BARHEMSYS for the prevention of PONV was evaluated in two randomized, double-blind, placebo-controlled, multi-center trials in patients undergoing general anesthesia and elective surgery (Study 1 and Study 2). In Study 1 (NCT01991860), patients received monotherapy with BARHEMSYS; while in Study 2 (NCT02337062), patients received BARHEMSYS in combination with one other intravenously administered, non-dopaminergic antiemetic (ondansetron, dexamethasone or betamethasone). In both trials, patients were administered BARHEMSYS at the induction of anesthesia.

Study 1 was conducted in the United States in 342 patients. The mean age was 54 years (range 21 to 88 years); 65% female; 87% White/Caucasian, 12% Black, and 1% Asian race. The treatment groups were similarly matched in terms of risk for PONV with 30% of patients having two risk factors, 47% of patients having three risk factors and 23% of patients having four risk factors.

Study 2 was conducted in the United States and Europe in 1,147 patients. The mean age was 49 years (range 18 to 91 years); 97% female; 75% White/Caucasian, 9% Black, 1% Asian, and 14% of unreported race. The treatment groups were similarly matched in terms of risk for PONV with 56% of patients having three risk factors and 43% of patients having four risk factors.

The primary efficacy endpoint in both trials was Complete Response, defined as absence of any episode of emesis or use of rescue medication within the first 24 hours postoperatively. Results for both trials are shown in Table 3.

Table 3. Complete Response Rates in Adult Patients for the Prevention of PONV Within 24 Hours After End of Surgery in Studies 1 and 2
 | Study 1 |  | Study 2
 | BARHEMSYS 5 mg (n=176) | Placebo (n=166) | BARHEMSYS 5 mg with Another Antiemetic (n=572) | Placebo with Another Antiemetic (n=575)
Complete Response | 78 (44%) | 54 (33%) | 330 (58%) | 268 (47%)
Difference (95% CI) [Unadjusted, nominal 95% confidence interval] | 12% (2%, 22%) |  | 11% (5%, 17%)

14.2 Treatment of Postoperative Nausea and Vomiting

The efficacy of BARHEMSYS 10 mg as a single dose was evaluated in two randomized, double-blind, placebo-controlled, multi-center trials in patients experiencing PONV after general anesthesia and elective surgery (Study 3 and Study 4). Study 3 (NCT02449291) enrolled patients who had not received prior PONV prophylaxis, whereas Study 4 (NCT02646566) included patients who had received and failed PONV prophylaxis with an antiemetic of another class. Patients were excluded if they had received a D2 receptor antagonist antiemetic.

Study 3 was conducted in 369 patients (mean age 47 years, range 19 to 82 years; 76% female; 82% White/Caucasian, 8% Black, 2% Asian, and 8% of unreported race). Most of the patients had either two risk factors (36%) or three risk factors (53%) for PONV and these percentages were similar between treatment groups.

Study 4 was conducted in 465 patients (mean age 46 years, range 18 to 85 years; 90% female; 82% White/Caucasian, 9% Black, 3% Asian, and 6% of unreported race). Patients had received prior PONV prophylaxis with one or more non-dopaminergic antiemetics: a 5-HT3-antagonist in 77%, dexamethasone in 65% and another antiemetic class in 10%. Most of the patients had either three risk factors (43%) or four risk factors (51%) for PONV and these percentages were similar between treatment groups.

For both trials, the primary efficacy endpoint was Complete Response defined as absence of any episode of emesis or use of rescue medication within the first 24 hours after treatment (excluding emesis within the first 30 minutes).

BARHEMSYS Complete Response in both studies is shown in Table 4.

Table 4. Complete Response Rates in Adult Patients for the Treatment of PONV Within 24 Hours After Treatment [Excluding emesis within the first 30 minutes] in Studies 3 and 4
 | Study 3 (no prophylaxis) |  | Study 4 (prior prophylaxis) [Received prior PONV prophylaxis with one or more non-dopaminergic antiemetics: a 5-HT3-antagonist in 77%, dexamethasone in 65% and another antiemetic class in 10%]
 | BARHEMSYS 10 mg (n=188) | Placebo (n=181) | BARHEMSYS 10 mg (n=230) | Placebo (n=235)
Complete Response | 59 (31%) | 39 (22%) | 96 (42%) | 67 (29%)
Difference (95% CI) [Unadjusted, nominal 95% confidence interval] | 10% (1%, 19%) |  | 13% (5%, 22%)

16 HOW SUPPLIED/STORAGE AND HANDLING

BARHEMSYS (amisulpride) injection is supplied as follows:

NDC 71390-125-20: Package of 10 cartons. Each carton (NDC 71390-125-21) contains one single-dose vial of clear, colorless, sterile solution of BARHEMSYS (amisulpride) injection, 5 mg in 2 mL (2.5 mg/mL).

NDC 71390-125-50: Package of 10 cartons. Each carton (NDC 71390-125-51) contains one single-dose vial of clear, colorless, sterile solution of BARHEMSYS (amisulpride) injection, 10 mg in 4 mL (2.5 mg/mL).

STORAGE AND HANDLING

Store vials at 20°C to 25°C (68°F to 77°F) [see USP Controlled Room Temperature].

Protect from light. Administer BARHEMSYS within 12 hours after the vial is removed from the protective carton [see Dosage and Administration (2.2)].

17 PATIENT COUNSELING INFORMATION

QT Prolongation

Instruct patients to contact their healthcare provider immediately if they perceive a change in their heart rate, if they feel lightheaded, or if they have a syncopal episode [see Warnings and Precautions (5.1)].

Drug Interactions

Advise patients to report to their healthcare provider if they are taking drugs which prolong the QT interval [see Warnings and Precautions (5.1)].

Lactation

Women may consider reducing infant exposure through pumping and discarding breastmilk for 48 hours after BARHEMSYS administration [see Use in Specific Populations (8.2)].

Distributed by Acacia Pharma Inc.
8440 Allison Pointe Blvd, Suite 100
Indianapolis, IN 46250 USA
© 2022 Acacia Pharma Inc. All rights reserved.
BAR-0005-USPI-09/2022

PRINCIPAL DISPLAY PANEL - 2 mL Vial Label

NDC 71390-125-21
Rx ONLY

Barhemsys®
(amisulpride) injection

5 mg | 2 mL
(2.5 mg/mL)

Single-dose sterile vial,
discard unused portion.

For Intravenous Infusion Only.

PRINCIPAL DISPLAY PANEL - 2 mL Vial Carton

NDC 71390-125-21

Barhemsys®
(amisulpride) injection

5 mg | 2 mL
(2.5 mg/mL)

Single-dose sterile vial.

For Intravenous
Infusion Only.

Discard Unused Portion.

Rx ONLY

PRINCIPAL DISPLAY PANEL - 4 mL Vial Label

NDC 71390-125-51
Rx ONLY

Barhemsys®
(amisulpride) injection

10 mg | 4 mL
(2.5 mg/mL)

Single-dose sterile vial,
discard unused portion.

For Intravenous Infusion Only.

PRINCIPAL DISPLAY PANEL - 4 mL Vial Carton

NDC 71390-125-51

Barhemsys®
(amisulpride) injection

10 mg | 4 mL
(2.5 mg/mL)

Single-dose sterile vial.

For Intravenous
Infusion Only.

Discard Unused Portion.

Rx ONLY